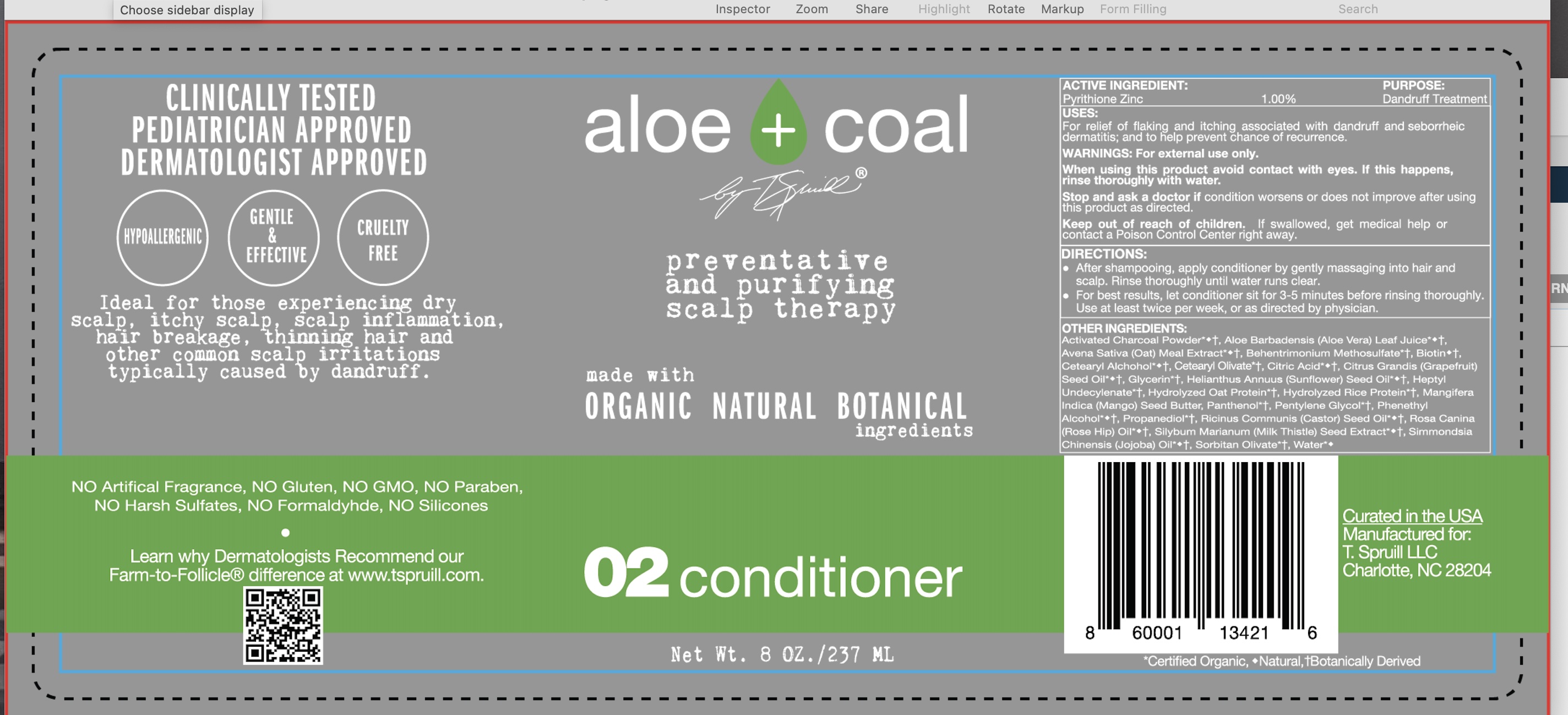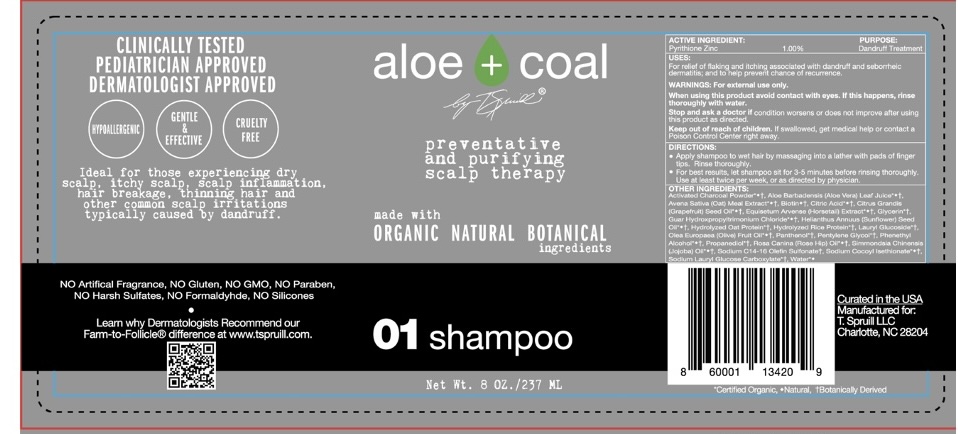 DRUG LABEL: Aloe Coal by T Spruill
NDC: 73324-002 | Form: LIQUID
Manufacturer: T. Spruill LLC.
Category: otc | Type: HUMAN OTC DRUG LABEL
Date: 20251229

ACTIVE INGREDIENTS: PYRITHIONE ZINC 1 g/100 mL
INACTIVE INGREDIENTS: ALOE VERA LEAF

WARNINGS

For external use only

Avoid contact with eyes

Stop use and ask a doctor if...

Keep out of reach of children

Keep out of reach of children. If swallowed, get medical help or contact a Poison Control Center right away.

PURPOSE

nti-dandruff

INACTIVE INGREDIENT

Water, Aloe Barbadensis Leaf Juice, Charcoal Powder, Glycerin, Cocamidopropyl Betaine, Sodium C14-16 Olefin Sulfonate, Citric Acid, Fragrance, Phenoxyethanol, Ethylhexylglycerin